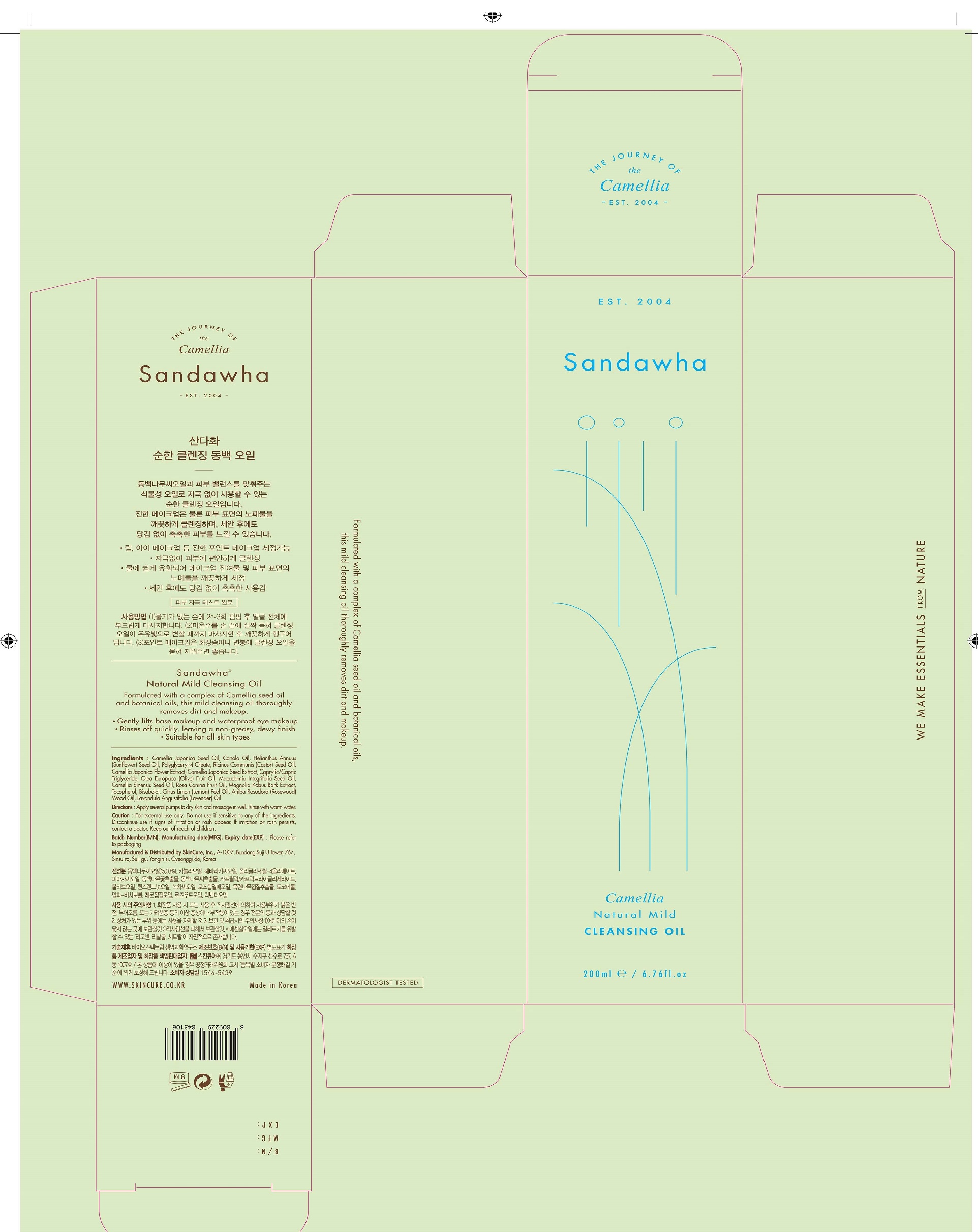 DRUG LABEL: Sandawha Natural Mild Cleansing Oil
NDC: 72289-0012 | Form: LIQUID
Manufacturer: SKINCURE INC
Category: otc | Type: HUMAN OTC DRUG LABEL
Date: 20201124

ACTIVE INGREDIENTS: CAMELLIA JAPONICA SEED OIL 15 g/100 mL
INACTIVE INGREDIENTS: CANOLA OIL; ROSA CANINA FRUIT OIL

Drug Facts

ACTIVE INGREDIENT

Camellia Japonica Seed Oil

INACTIVE INGREDIENT

Dongbakex
Camellia Japonica Flower Extract 28.0300
Camellia Japonica Seed Extract
Caprylic/Capric Triglyceride
Camellia Sinensis Seed Oil
Canola Oil 15.0000
Helianthus Annuus (Sunflower) Seed Oil 15.0000
Polyglyceryl-4 Oleate 14.0000
Ricinus Communis (Castor) Seed Oil 10.0000
Macadamia Integrifolia Seed Oil 1.0000
Olea Europaea (Olive) Fruit Oil 1.0000
Rosa Canina Fruit Oil 0.1000
MultiOil OilSoother
Olea Europaea (Olive) Fruit Oil 0.1000
Camellia Japonica Seed Oil
Tocopherol
Bisabolol
Rosa Canina Fruit Oil
Magnolia Kobus Bark Extract 0.0200
Citrus Limon (Lemon) Peel Oil 0.3750
Aniba Rosodora (Rosewood) Wood Oil 0.2250
Lavandula Angustifolia (Lavender) Oil 0.1500

PURPOSE

formulated with a complex of camellia seed oil and botanical oils, this mild cleansing oil thoroughly removes dirt and makeup

keep out of reach of the children

INDICATIONS AND USAGE

Apply several pumps to dry skin and massage in well. Rinse with warm water.

WARNINGS

for external use only

do not use if sensitive to any of the ingredients

discontinue use if signs of irritation or rash appear

if irritation or rash persists, contact a doctor

DOSAGE AND ADMINISTRATION

for external use only